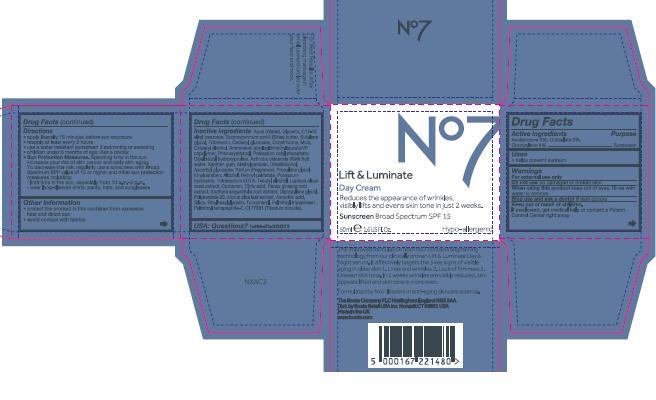 DRUG LABEL: No7 Lift and Luminate Day Cream SPF 15
NDC: 11489-091 | Form: CREAM
Manufacturer: BCM Ltd
Category: otc | Type: HUMAN OTC DRUG LABEL
Date: 20151010

ACTIVE INGREDIENTS: AVOBENZONE 1.5 g/50 g; OCTOCRYLENE 2 g/50 g; OCTISALATE 1 g/50 g
INACTIVE INGREDIENTS: WATER; GLYCERIN; C12-15 ALKYL BENZOATE; DIMETHICONE; MICA; CETEARYL GLUCOSIDE; TRIBEHENIN; AMMONIUM ACRYLOYLDIMETHYLTAURATE/VP COPOLYMER; PHENOXYETHANOL; DIPALMITOYL HYDROXYPROLINE; ALCOHOL; SHEA BUTTER; POTASSIUM CETYL PHOSPHATE; CITRIC ACID ACETATE; BUTYLENE GLYCOL; METHYLPARABEN; ETHYLPARABEN; XANTHAN GUM; DIPROPYLENE GLYCOL; VITAMIN A PALMITATE; ASCORBYL GLUCOSIDE; EDETATE SODIUM; TERT-BUTYL ALCOHOL; PANAX GINSENG ROOT OIL; LUPINUS ALBUS SEED; POLYSORBATE 20; POTASSIUM HYDROXIDE; ETHYLHEXYLGLYCERIN; TOCOPHEROL; ASCORBIC ACID; TITANIUM DIOXIDE; PALMITOYL TETRAPEPTIDE-7

No7 Lift and Luminate Day Cream SPF 15

Carton Active Ingredients Section

Active ingredients

Avobenzone 3%

Octisalate 2%

Octocrylene 4%

Uses

Uses - helps prevent sunburn

Warnings

For external use only

Do not use on damaged or broken skin

When using this product keep out of eyes. Rinse with water to remove.

Ask a doctor

Stop use and ask a doctor if rash occurs

Keep out of reach of children

If swallowed, get medical help or contact a Poison Control Center right away

Directions

Apply liberally 15 minutes before sun exposure

reapply at least every 2 hours

use a water resistant sunscreen if swimming or sweating

children under 6 months of age: Ask a doctor

Sun Protection Measures. Spending time in the sun increases your risk of skin cancer and early skin aging.

To decrease this risk, regularly use a sunscreen with a Broad Spectrum SPF value of 15 or higher and other sun protection measures including:

Limit time in the sun, especially from 10 a.m - 2 p.m.

wear long-sleeved shirts,pants,hats and sunglasses.

Storage

Other information

Protect the product in this container from excessive heat and direct sun

Avoid contact with fabrics

Inactive ingredients

Aqua(Water), Glycerin, C12-15 alkyl benzoate, Dimethicone, Mica, Cetearyl glucoside, Tribehenin, Ammonium acryloydimethyltaurate/VP copolymer, Phenoxyethanol, Dipalmitoyl hydroxyproline, Alcohol, Butyrospermum parkii (Shea) butter, Potassium cetyl phosphate, Actinidia chinensis(Kiwi) fruit water, Cetearyl alcohol, Butylene glycol, Dimethiconol, Methylparaben, Parfum(Fragrance), Propylene glycol, Xanthan gum, Ethylparaben, Dipropylene glycol, Retinyl palmitate, Ascorbyl glucoside,, Tetrasodium EDTA, T-butyl alcohol, Lupinus albus seed extract, Carbomer, Citric acid, Panax ginseng root extract, Sophora angustifolia root extract,Polysorbate 20, Morus alba leaf extract, Ascorbic acid, Potassium hydroxide, Ethylhexylglycerin, Silica, Tocopherol, Palmitoyl tripeptide-1, Palmitoyl tetrapeptide-7, CI 77891(Titanium dioxide)

DESCRIPTION

Reduces the appearance of wrinkles, visibly lifts and evens skin tone in just 2 weeks. The improved formulation from No7 contains brightening technology from our clinically proven Lift and Luminate Day and Night serum. It effectively targets the 3 key signs of visible aging in older skin. 1.Lines and wrinkles 2. Lack of firmness 3. Uneven skin tone. In 2 weeks wrinkles are visbly reduced, skin appears lifted and skn tone is more even.

Formulated by No7, leaders in antiaging skin care science

For Best Results: After cleansing massage in small upward circles over your face and neck

PATIENT COUNSELING INFORMATION

Made in the UK

The Boots Company PLC Nottingham England NG2 3AA

Dist. by Boots Retail USA Inc. Norwalk CT 06851 USA

www.boots.com